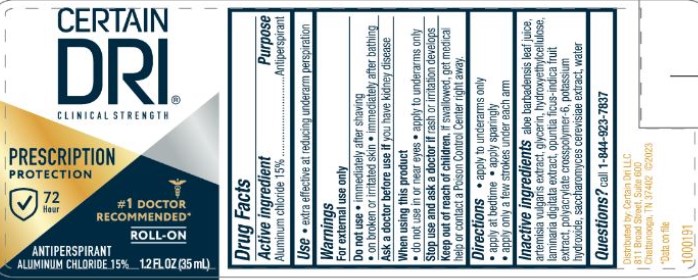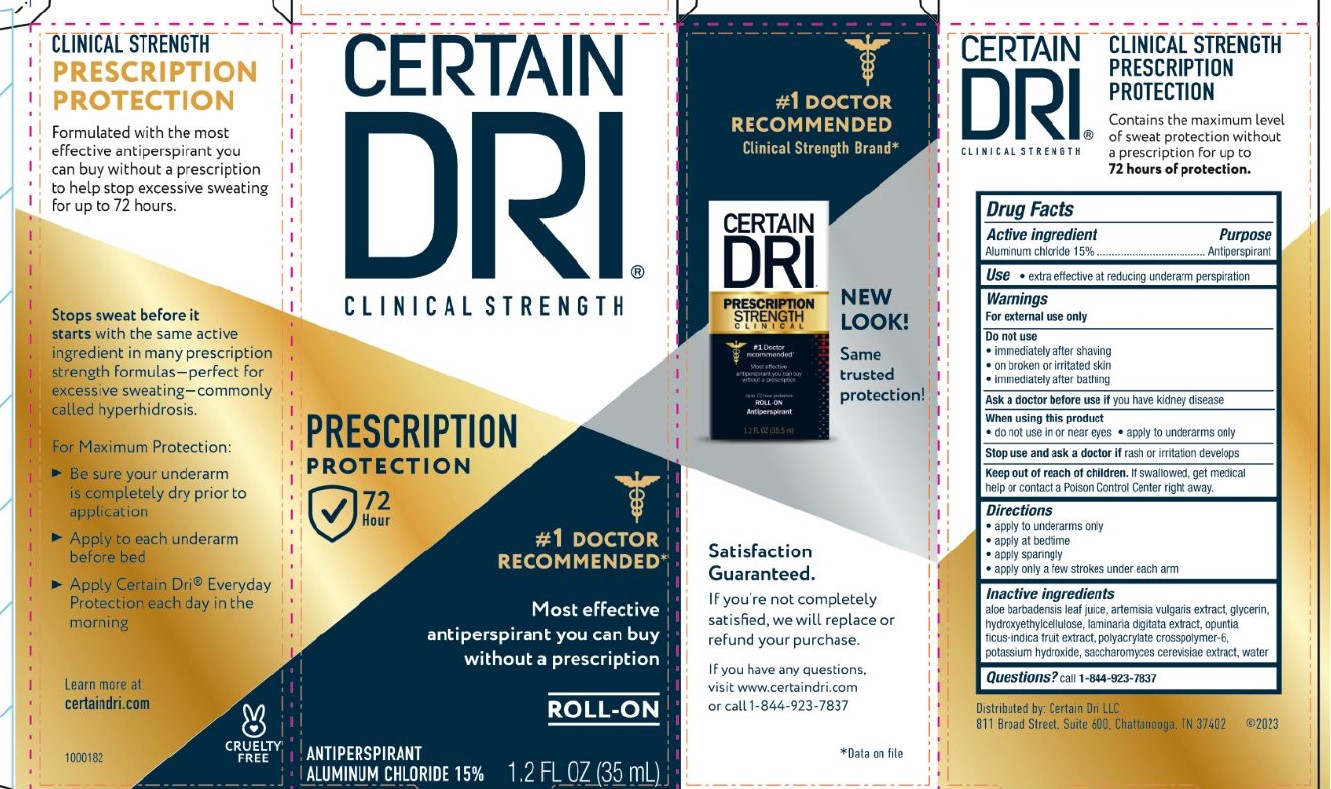 DRUG LABEL: Certain Dri Clinical Strength Roll On
NDC: 69693-724 | Form: FOR SOLUTION
Manufacturer: Clarion Brands, LLC
Category: otc | Type: HUMAN OTC DRUG LABEL
Date: 20251223

ACTIVE INGREDIENTS: ALUMINUM CHLORIDE 0.15 g/100 mL
INACTIVE INGREDIENTS: ALOE; ARTEMISIA VULGARIS WHOLE; GLYCERIN; CETYL HYDROXYETHYLCELLULOSE (350000 MW); LAMINARIA DIGITATA; OPUNTIA FICUS-INDICA FLOWER; POLYACRYLATE-1 CROSSPOLYMER; POTASSIUM HYDROXIDE; SACCHAROMYCES CEREVISIAE; WATER

Drug Facts

Active Ingredient

Aluminum chloride 15%

Purpose

Antiperspirant

Use

- extra effective at reducing underarm perspiration

Warnings

For external use only

Do not use

- immediately after shaving
- on broken or irritated skin
- immediately after bathing

Ask a doctor beforeuse if you have kidney disease

When using this product

- do not use in or near eyes
- apply to underarms only

Stop use and ask a doctor ifrash or irritation develops

Keep out of reach of children.If swallowed, get medical help or contact a Poison Control Center right away.

Directions

- apply to underarms only
- apply at bedtime
- apply sparingly
- apply only a few strokes under each arm

Inactive ingredients

aloe barbadensis leaf juice, artemisia vulgarixs extract, glycerin, hydroxyethylcelluse, laminaria digitata extract, opuntia ficus-indica fruit extract, polyacrylate crosspolymer-6, potassium hydroxide, saccharomyces cerevislae extract, water

Questions?call 1-844-923-7837

PACKAGE LABEL.PRINCIPAL DISPLAY PANEL

CERTAIN
DRI®
CLINICAL STRENGTH
PRESCRIPTION
PROTECTION
72 Hour
#1 DOCTOR
RECOMENDED*
Most effective
antiperspirant you can buy
without a prescription
ROLL-ON
ANTIPERSPIRANT
ALUMINUM CHLORIDE 15% 1.2 FL OZ (35 mL)

#1 DOCTOR
RECOMMENDED
Clinical Strength Brand*
NEW
LOOK!
Same
trusted
protection!
Satisfaction
Guaranteed.
If you're not completely
satisfied, we will replace or
refund your purchase.
If you have any questions,
visit www.certaindri.com
or call 1-844-923-7837
*Data on file
Formulated with the most
effective antiperspirant you
can buy without a prescription
to help stop excessive sweating
for up to 72 hours.
Stop sweat before it
starts with the same active
ingredient in many prescription
strength formulas - perfect for
excessive sweating - commonly
called hyperhidrosis.
for Maximum Protection:

- Be sure your underarm
  is completely dry prior to
  application
- Apply to each underarm
  before bed
- Apply Certain Dri®Everyday
  Protection each day in the
  morning

Learn more at
certaindri.com
1000182
CRUELTY FREE
Distributed by: Certain Dri LLC
811 Broad Street, Suite 600
Chattanooga, TN 37402 ©2023

1000191